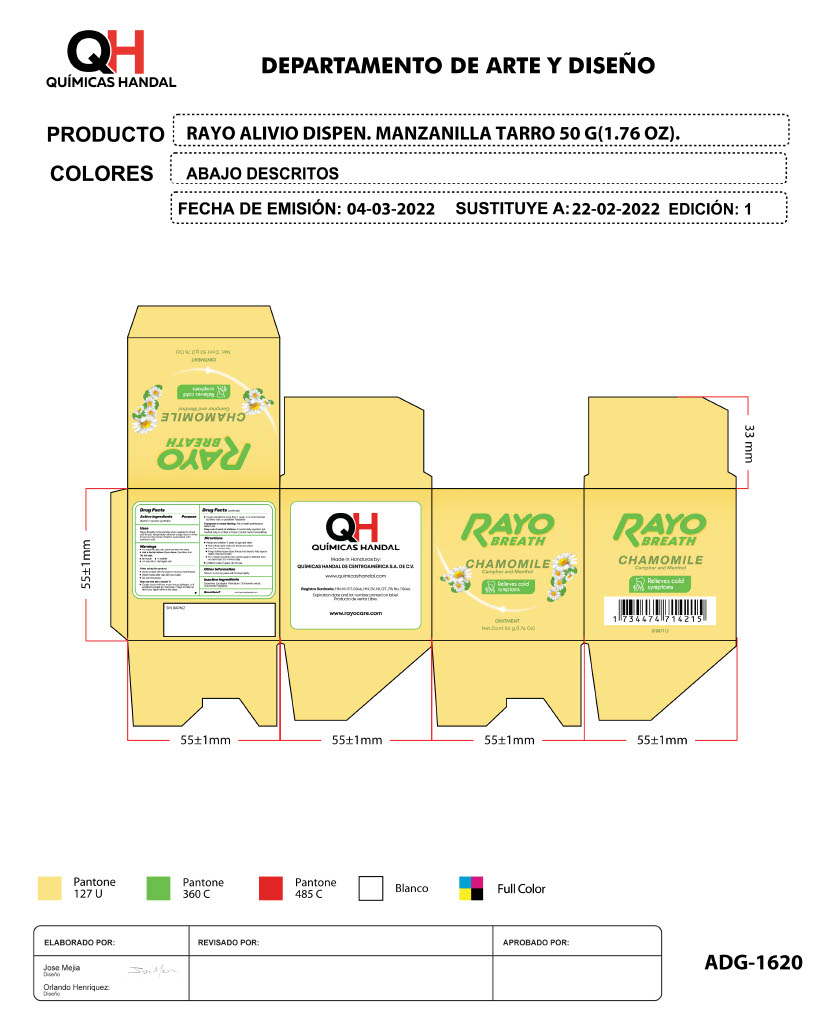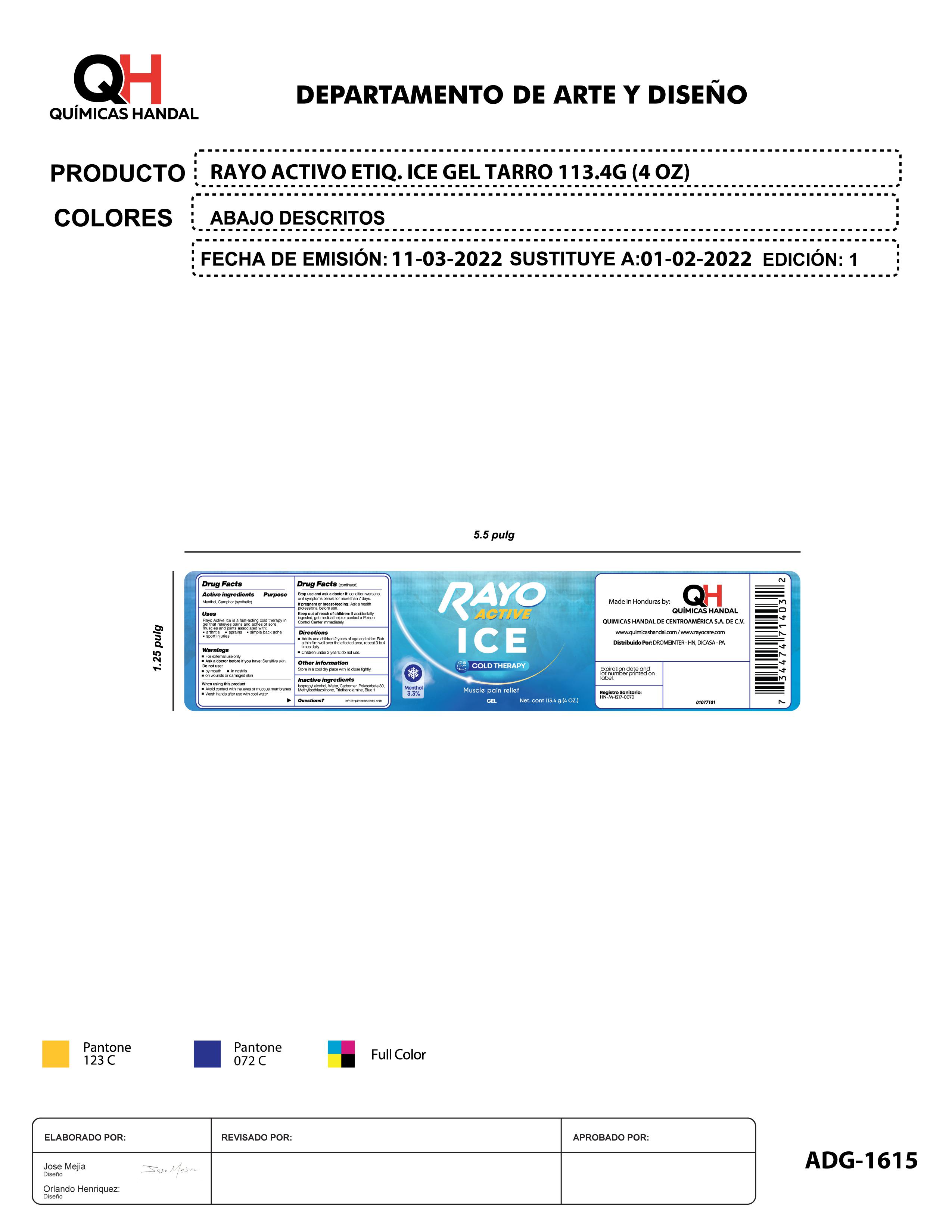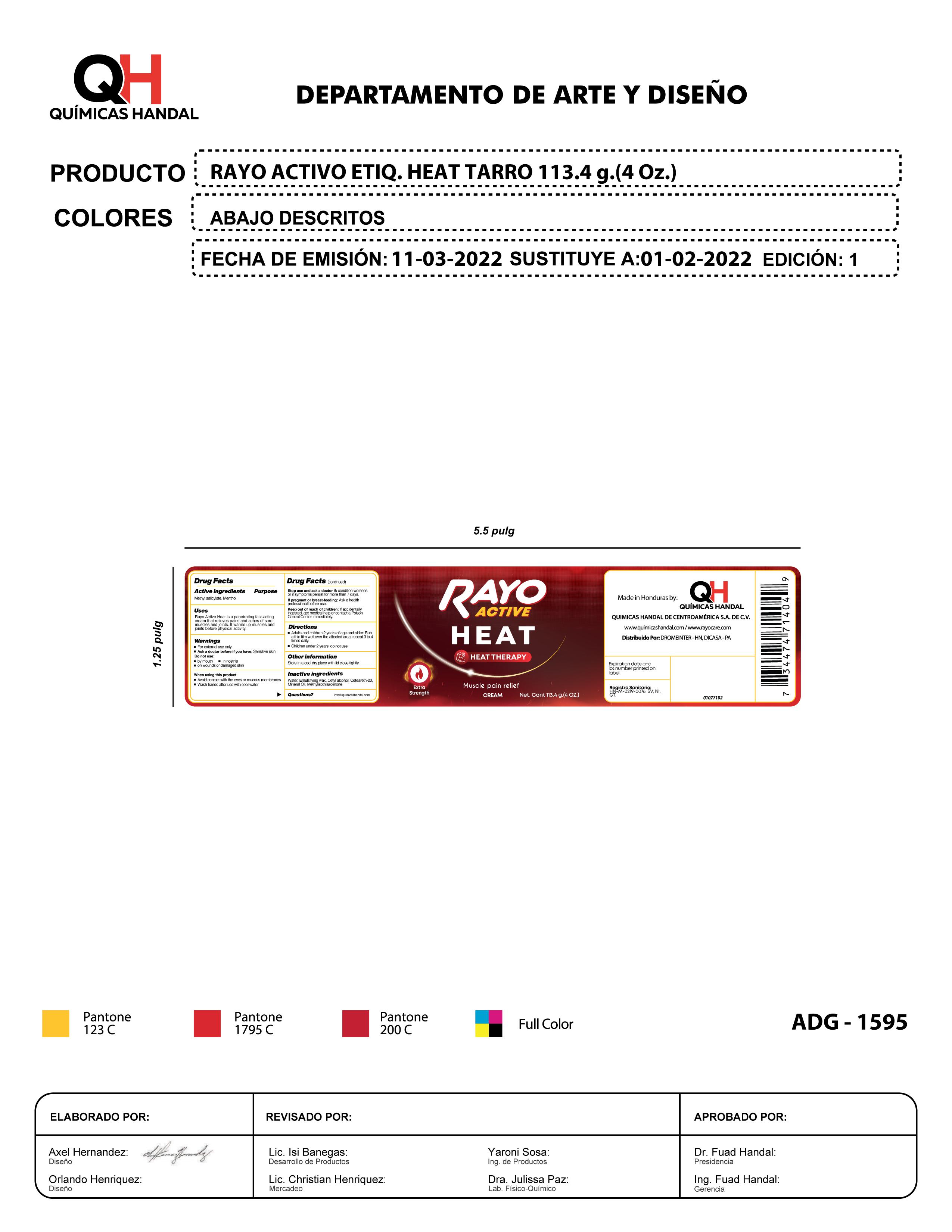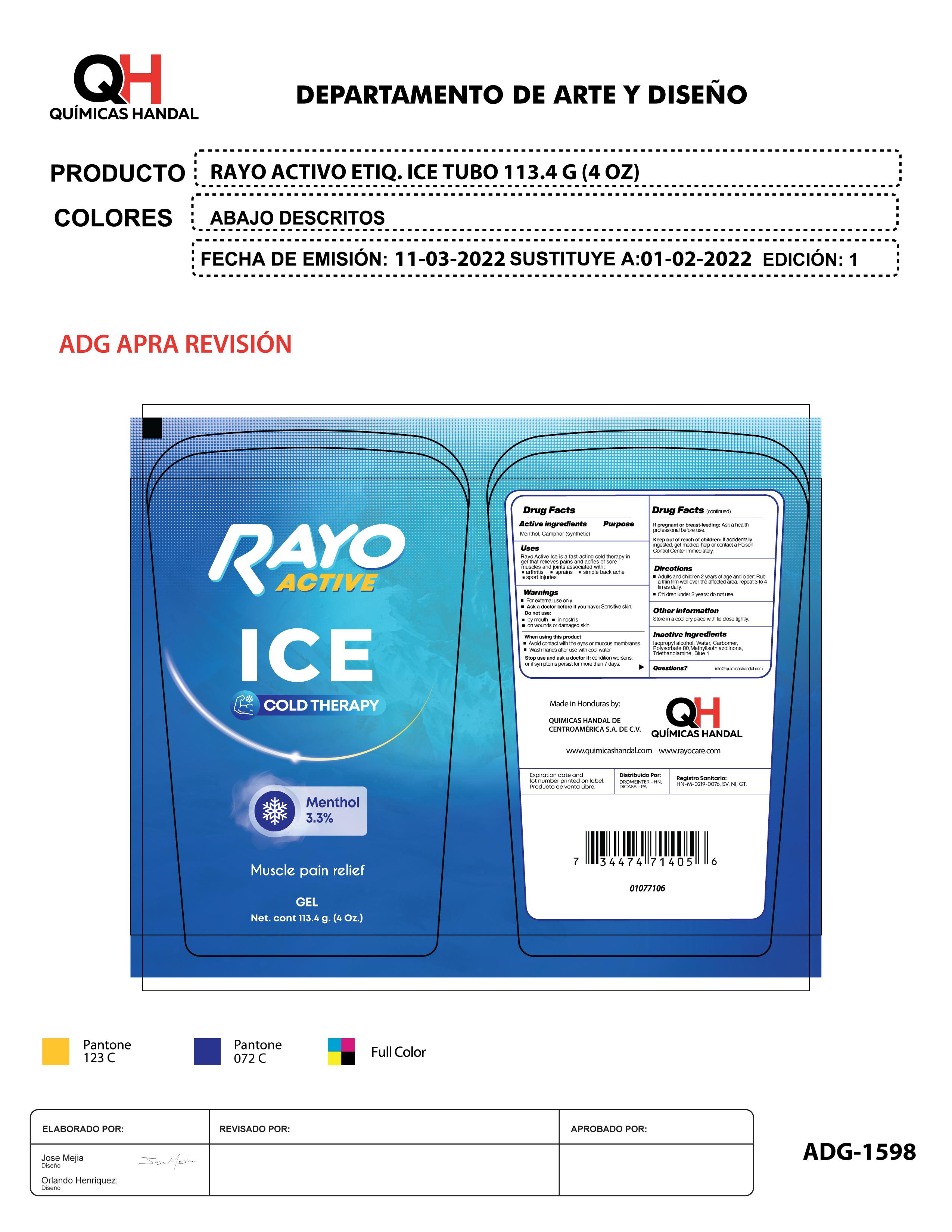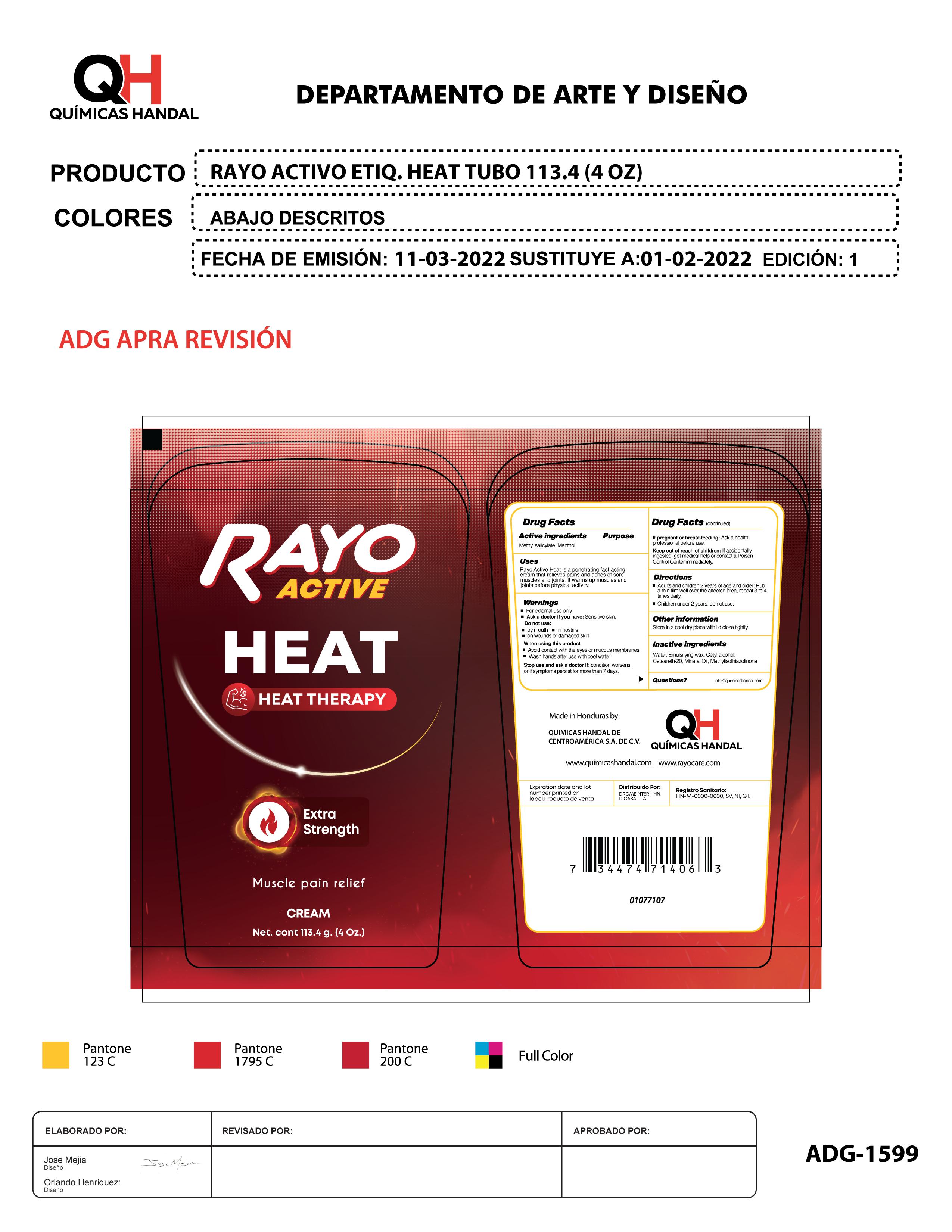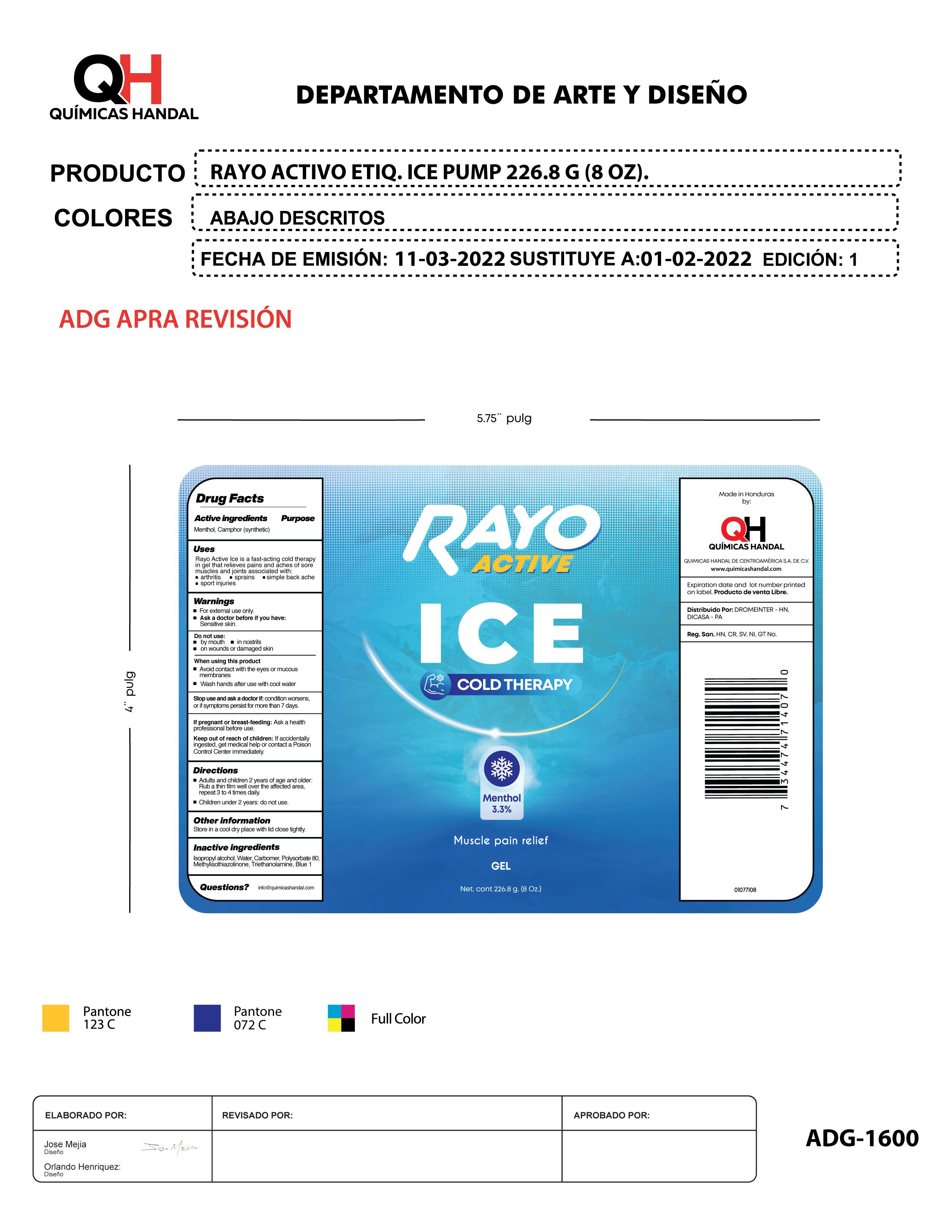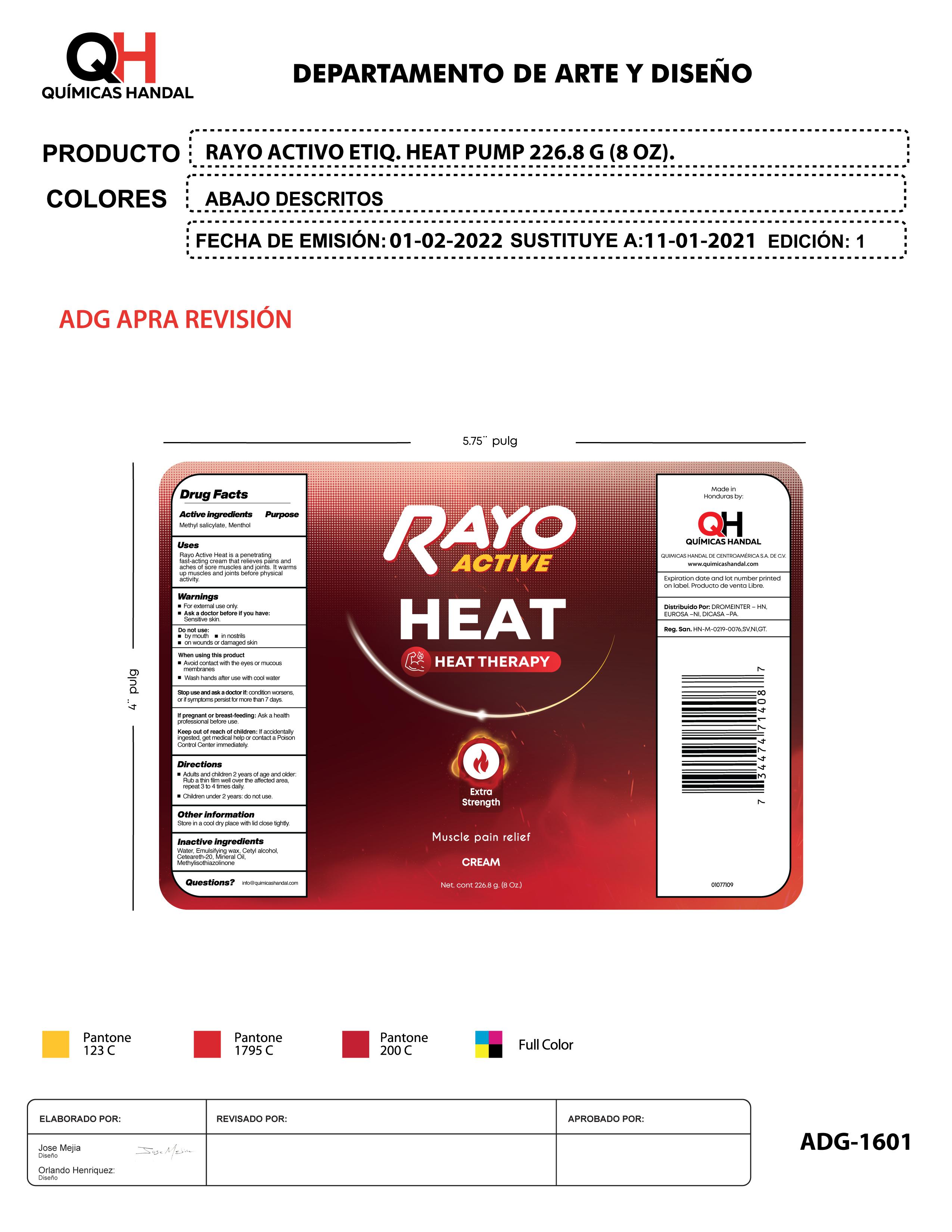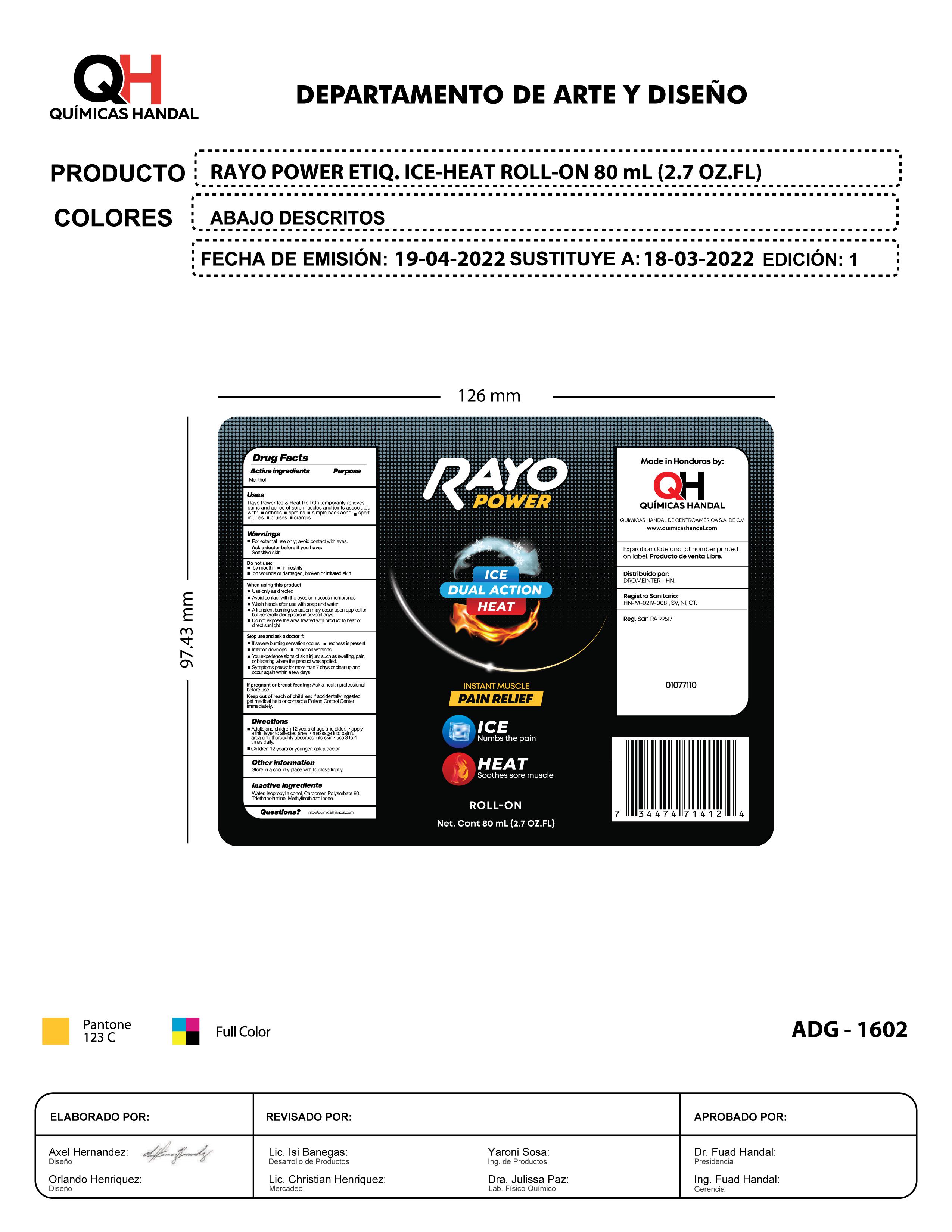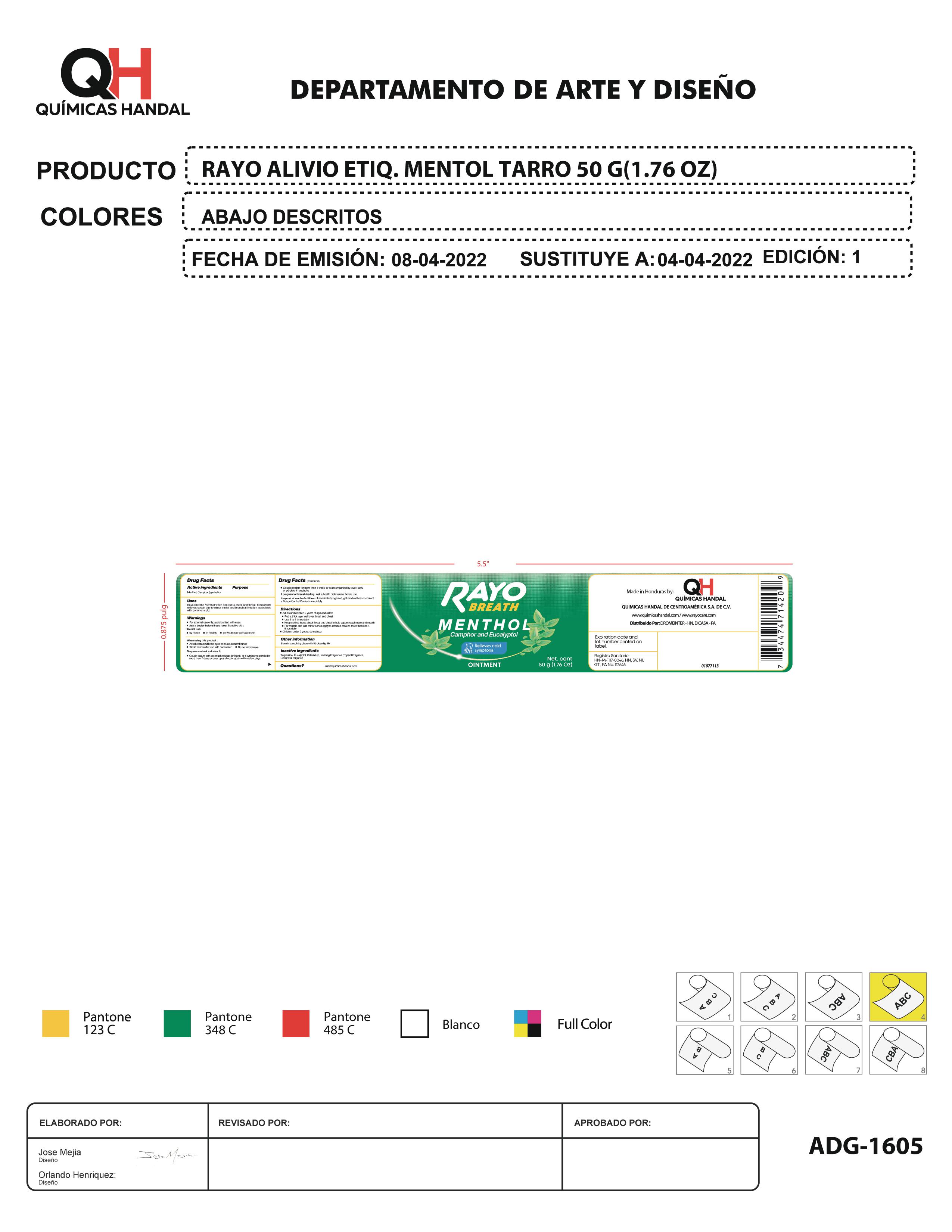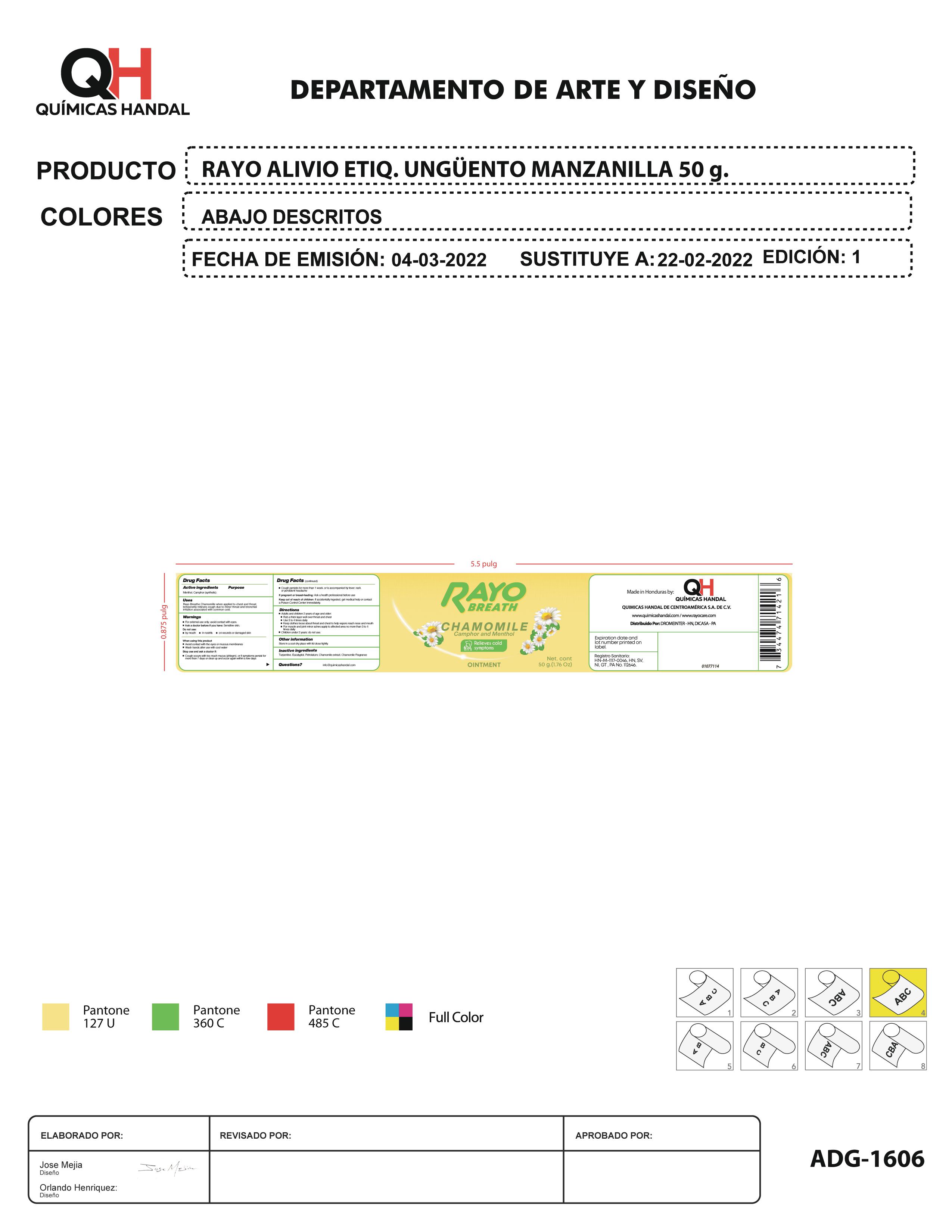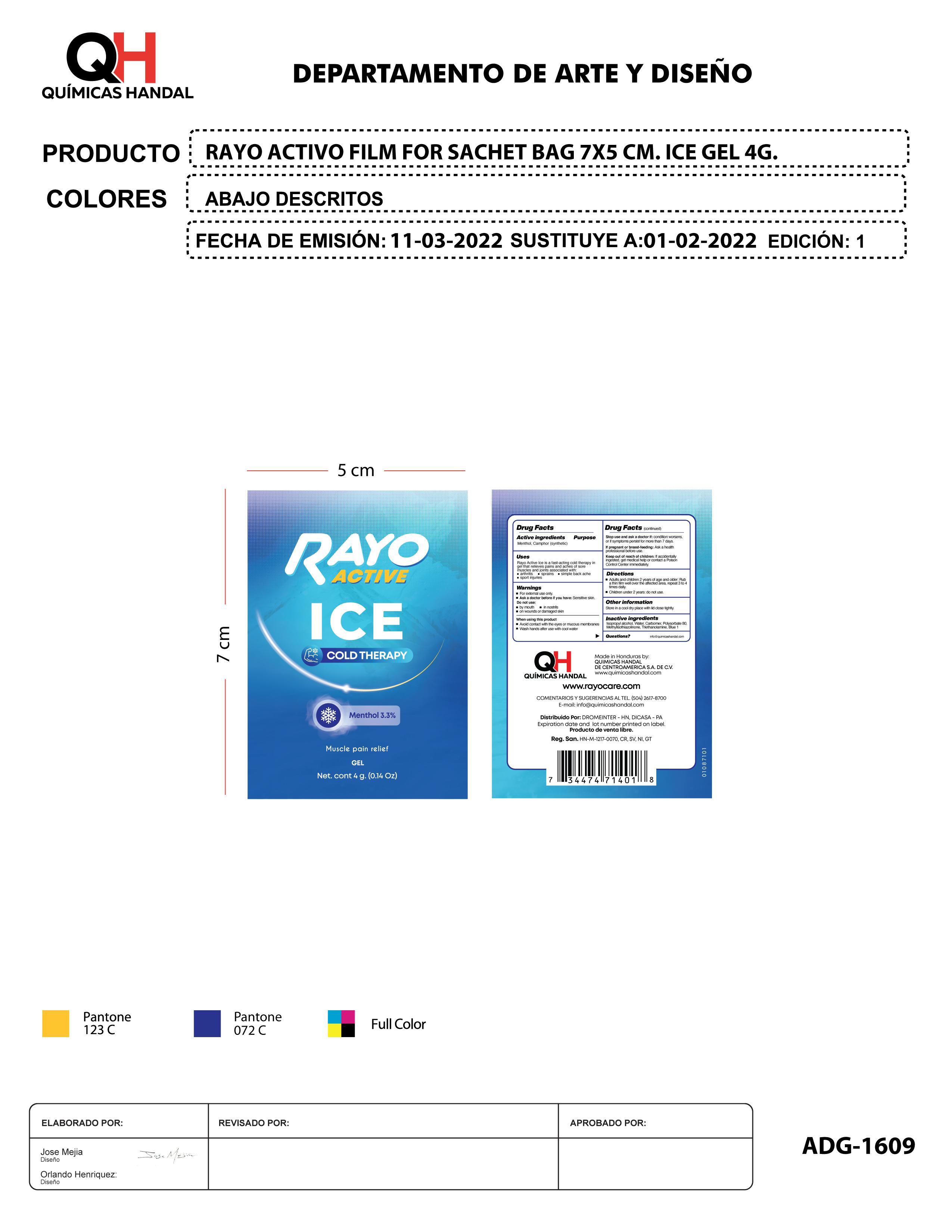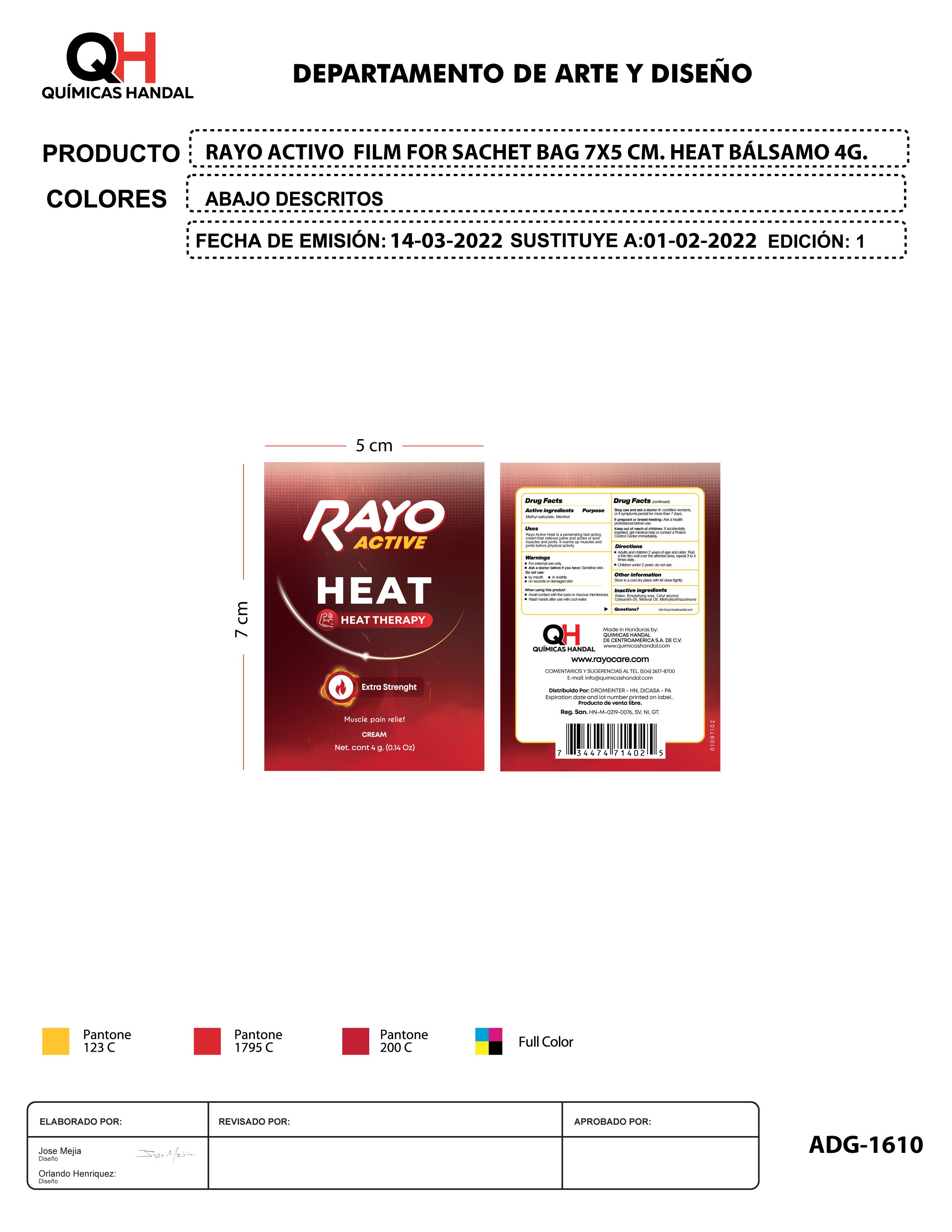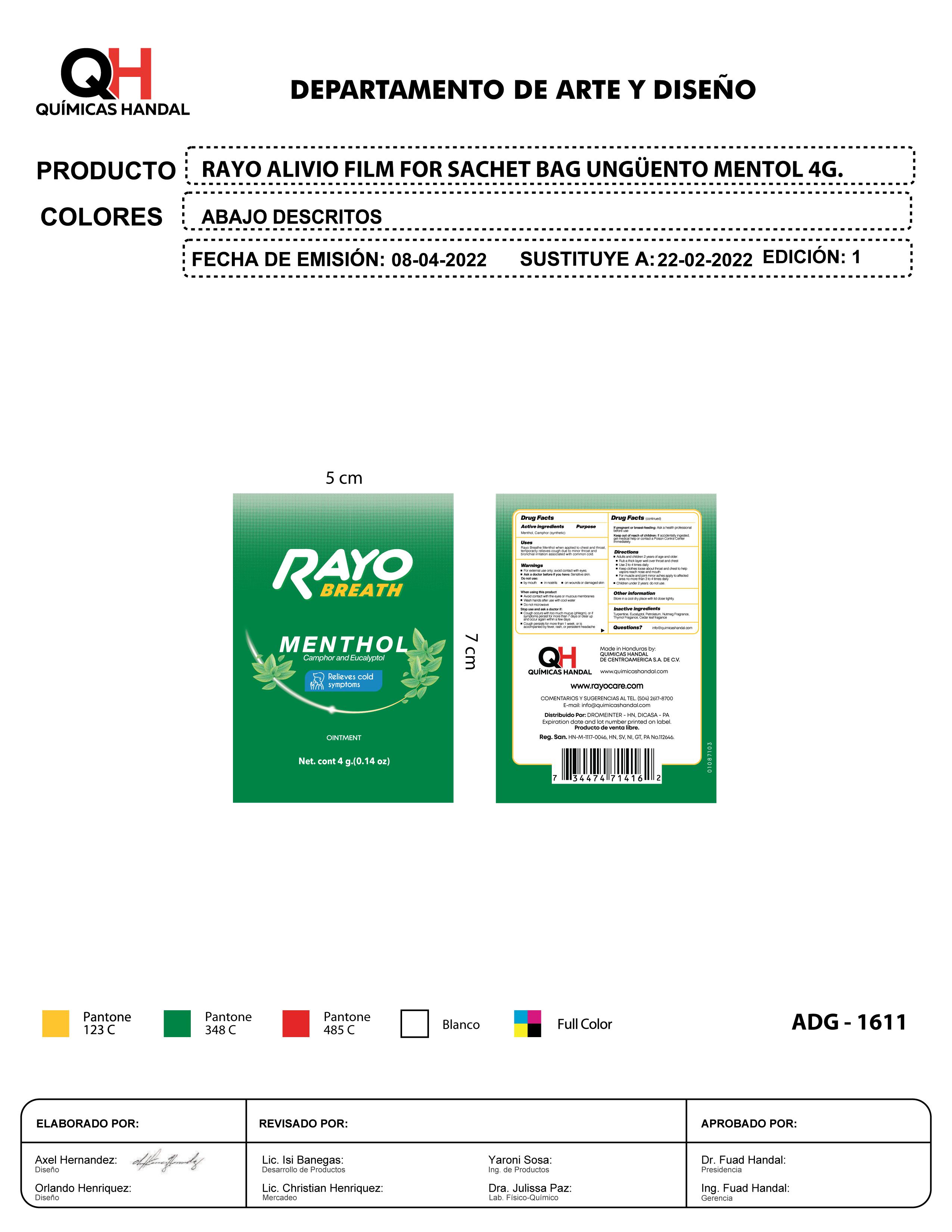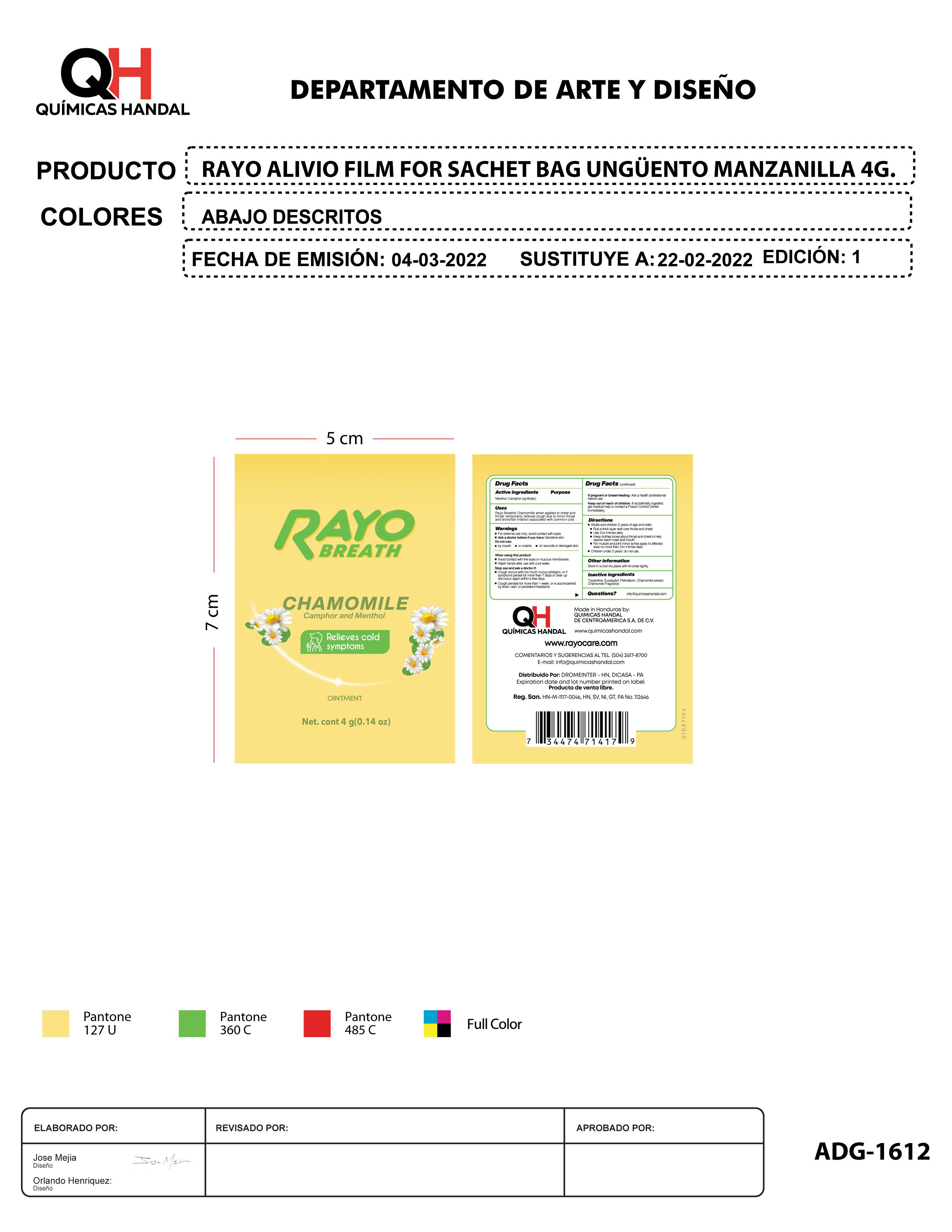 DRUG LABEL: RAYO ACTIVE HEAT
NDC: 83033-1610 | Form: CREAM
Manufacturer: Quimicas Handal de Centroamerica SA de CV
Category: otc | Type: HUMAN OTC DRUG LABEL
Date: 20260122

ACTIVE INGREDIENTS: MENTHOL 1 g/1 g; METHYL SALICYLATE 1 g/1 g
INACTIVE INGREDIENTS: MICROCRYSTALLINE WAX 1 g/1 g; WATER 1 g/1 g; MINERAL OIL 1 g/1 g; CETYL ALCOHOL 1 g/1 g; POLYOXYL 20 CETOSTEARYL ETHER 1 g/1 g; METHYLISOTHIAZOLINONE 1 g/1 g

Directions

- Adults and children 2 years of age and older:

1. Rub a thick layer well over throat and chest
2. Use 3 to 4 times daily
3. Keep clothes loose about throat and chest to help vapors reach nose and mouth
4. For muscle and joint minor aches apply to affected area no more than 3 to 4 times daily

- Children under 2 years: do not use.

WARNINGS

- For external use only; avoid contact with eyes
- Ask a doctor before if you have: sensitive skin

Do not use

- by mouth
- in nostrils
- on wounds or damaged skin

When using this product

- Avoid contact with the ayes or muccus membranes
- Wash hands after use with cool water
- Do not microwave

Stop use and ask a doctor if:

- Cough occurs with too much mucus (phlegm), or if symptoms persist for more than 7 days or clear up and occur again within a few days.

INACTIVE INGREDIENT

T

Directions

Adults and children 2 years of age and older:

Rub a thick layer well over throat and chest
Use 3 to 4 times daily
Keep clothes loose about throat and chest to help vapors reach nose and mouth
For muscle and joint minor aches apply to affected area no more than 3 to 4 times daily

Children under 2 years: do not use.

Keep out of reach of children: If accidentally ingested, get medical help or contact a Poison Control Center immediately.

PURPOSE

When applied to chest and throat, temporarily relieves cough due to minor throat and bronchial irritation associated with common cold.

ACTIVE INGREDIENT

Mentol, Camphor (synthetic)

QUESTIONS

info@quimicashandal.com